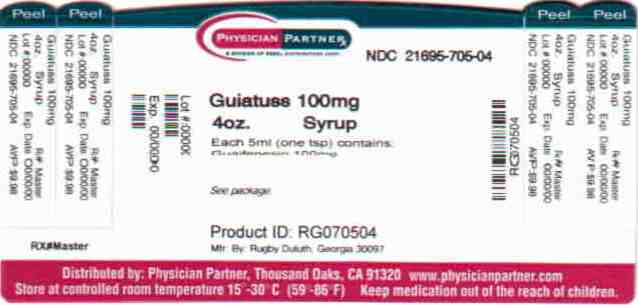 DRUG LABEL: Cough
NDC: 21695-705 | Form: LIQUID
Manufacturer: Rebel Distributors Corp
Category: otc | Type: HUMAN OTC DRUG LABEL
Date: 20110209

ACTIVE INGREDIENTS: Guaifenesin 100 mg/5 mL
INACTIVE INGREDIENTS: Caramel; Citric Acid Monohydrate; Corn Syrup; FD&C RED NO. 40; Glycerin; Menthol; Propylene Glycol; Water; Sodium Benzoate; Saccharin Sodium

Rugby®
Cough
SYRUP

Active ingredient (in each 5 mL teaspoonful)

Guaifenesin 100 mg

Uses

helps loosen phlegm and thin bronchial secretions to rid the bronchial passageways of bothersome mucus

Warnings

Ask a doctor before use if you have

- a cough with too much phlegm (mucus)
- a persistent or chronic cough as occurs with smoking, asthma, chronic bronchitis, or emphysema

Stop use and ask a doctor if cough lasts more than 7 days, comes back, or occurs with fever, rash, or headache that lasts. These could be signs of a serious condition.

PREGNANCY OR BREAST FEEDING

If pregnant or breast-feeding, ask a health professional before use.

Keep out of reach of children. In case of overdose, get medical help or contact a Poison Control Center right away.

Directions

- take every four hours
- do not take more than 6 doses in 24 hours

adults and children 12 years and over | 2–4 teaspoonfuls
children 6 to under 12 years | 1–2 teaspoonfuls
children under 6 years | do not use

Other information

- each teaspoonful contains: sodium 3 mg
- store at room temperature 15°–30°C (59°–86°F)

Inactive ingredients

caramel powder, citric acid, corn syrup, FD&C red #40, glycerin, menthol, propylene glycol, purified water, saccharin sodium, sodium benzoate

QUESTIONS

1-800-645-2158, 9 am – 5 pm ET, Monday – Friday

TAMPER EVIDENT

DO NOT USE IF INNER FOIL SEAL OVER MOUTH OF BOTTLE IS BROKEN OR MISSING

PRINCIPAL DISPLAY PANEL - 118 mL Bottle Label

Rebel Distributors Corp
NDC 21695-705-04

- FOR ADULTS AND CHILDREN
- NON-NARCOTIC EXPECTORANT
- ALCOHOL FREE

Cough
SYRUP
Guaifenesin, USP

4 fl oz (118 mL)